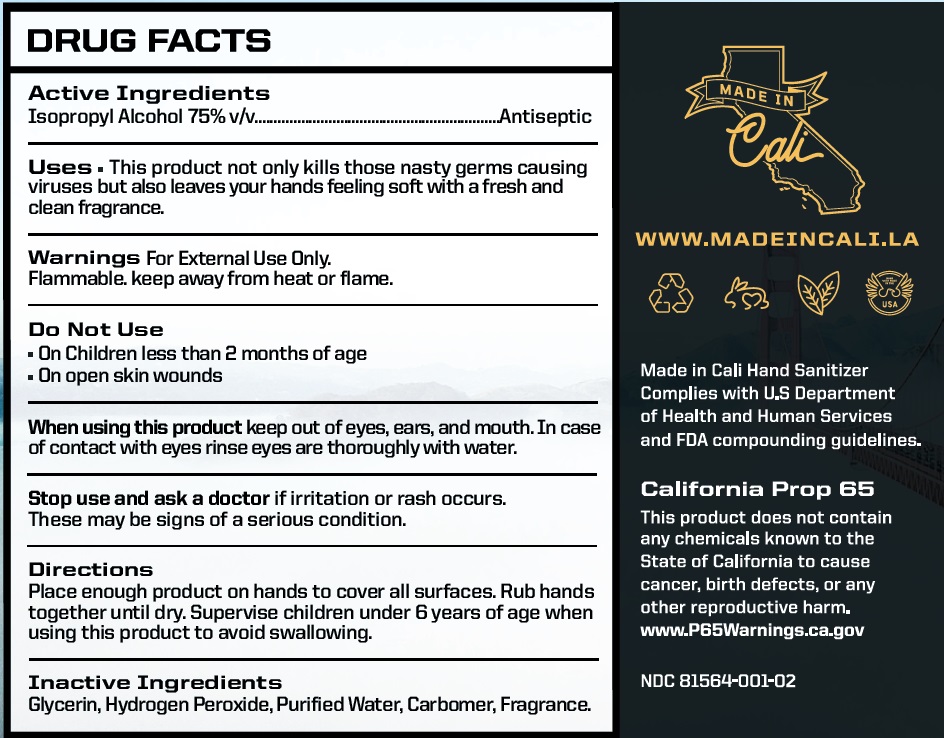 DRUG LABEL: MadeinCali Hand Sanitizer
NDC: 81564-001 | Form: GEL
Manufacturer: MADE IN CALI LLC
Category: otc | Type: HUMAN OTC DRUG LABEL
Date: 20210216

ACTIVE INGREDIENTS: ISOPROPYL ALCOHOL 75 mL/100 mL
INACTIVE INGREDIENTS: GLYCERIN; HYDROGEN PEROXIDE; WATER; CARBOMER HOMOPOLYMER, UNSPECIFIED TYPE

MadeinCali Hand Sanitizer

Active Ingredients

Isopropyl Alcohol 75% v/v

Purpose

Antiseptic

Uses

This product not only kill those nasty germs causing viruses but also leaves your hands feeling soft with a fresh and clean fragrance.

Warnings

For External Use Only.

Flammable: keep away from heat or flame.

Do Not Use

- On Children less than 2 months of age
- On open skin wounds

When using this product keep out of eyes, ears, and mouth. In case of contact with eyes rinse eyes are thoroughly with water.

Stop use and ask a doctor if irritation or rash occurs. These may be signs of a serious condition.

Keep out of reach of children. If swallowed, get medical help or contact a poison control center right away.

Directions

Place enough product on hands to cover all surfaces. Rub hands together until dry.

Supervise children under 6 years of age when using this product to avoid swallowing.

Inactive Ingredients

Glycerine, Hydrogen Peroxide, Purified Water, Carbomer, Fragrance

Distributed by

MADE IN CALI LLC

1621 Boyd St, Santa Ana, CA 92705

Made in USA